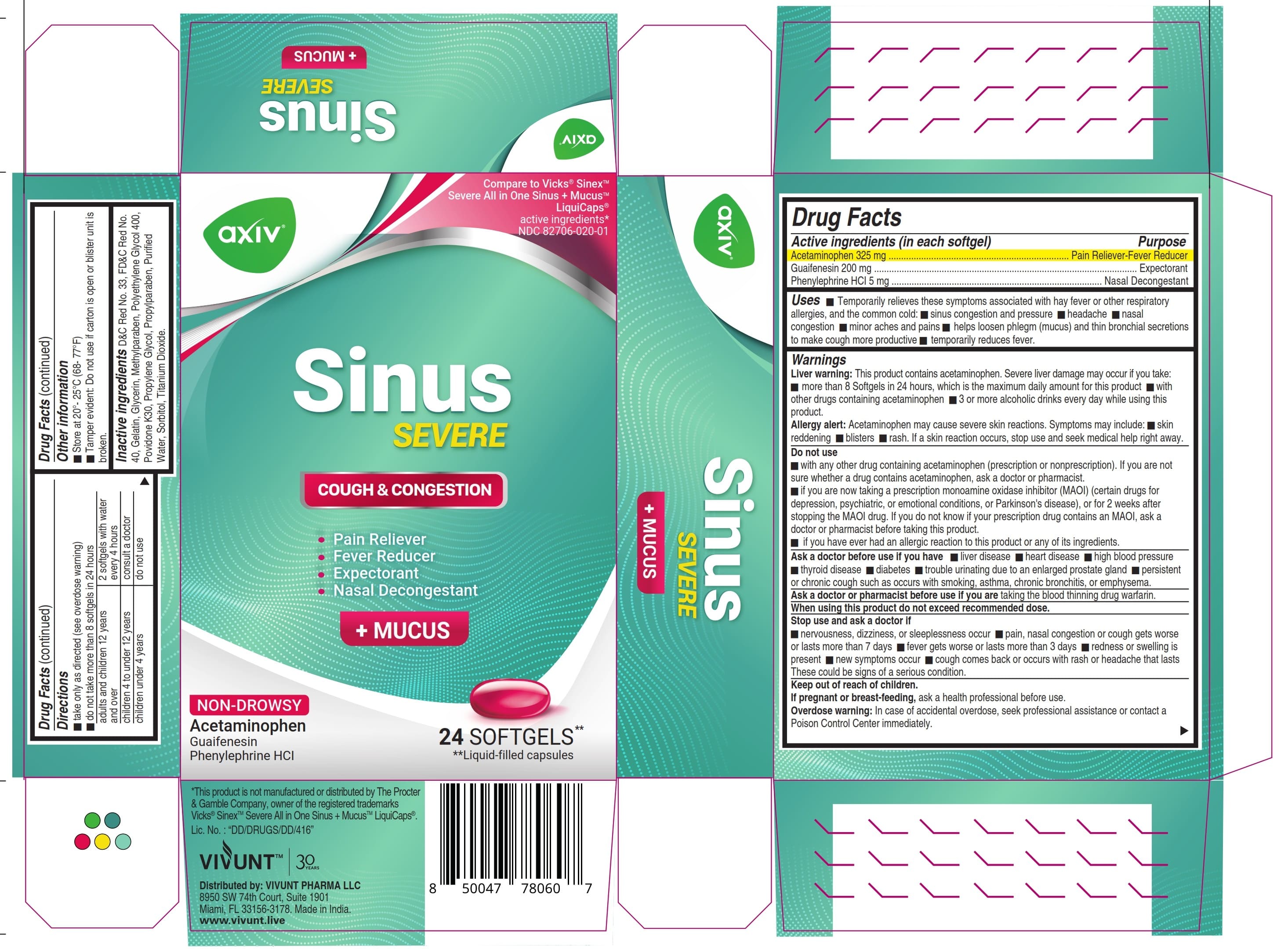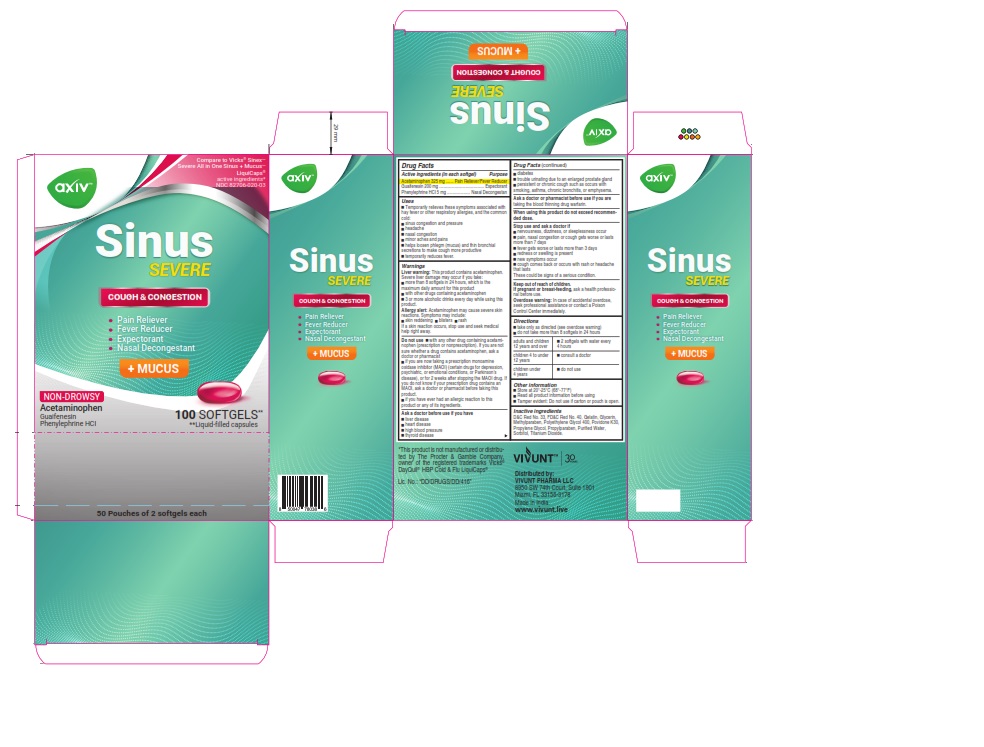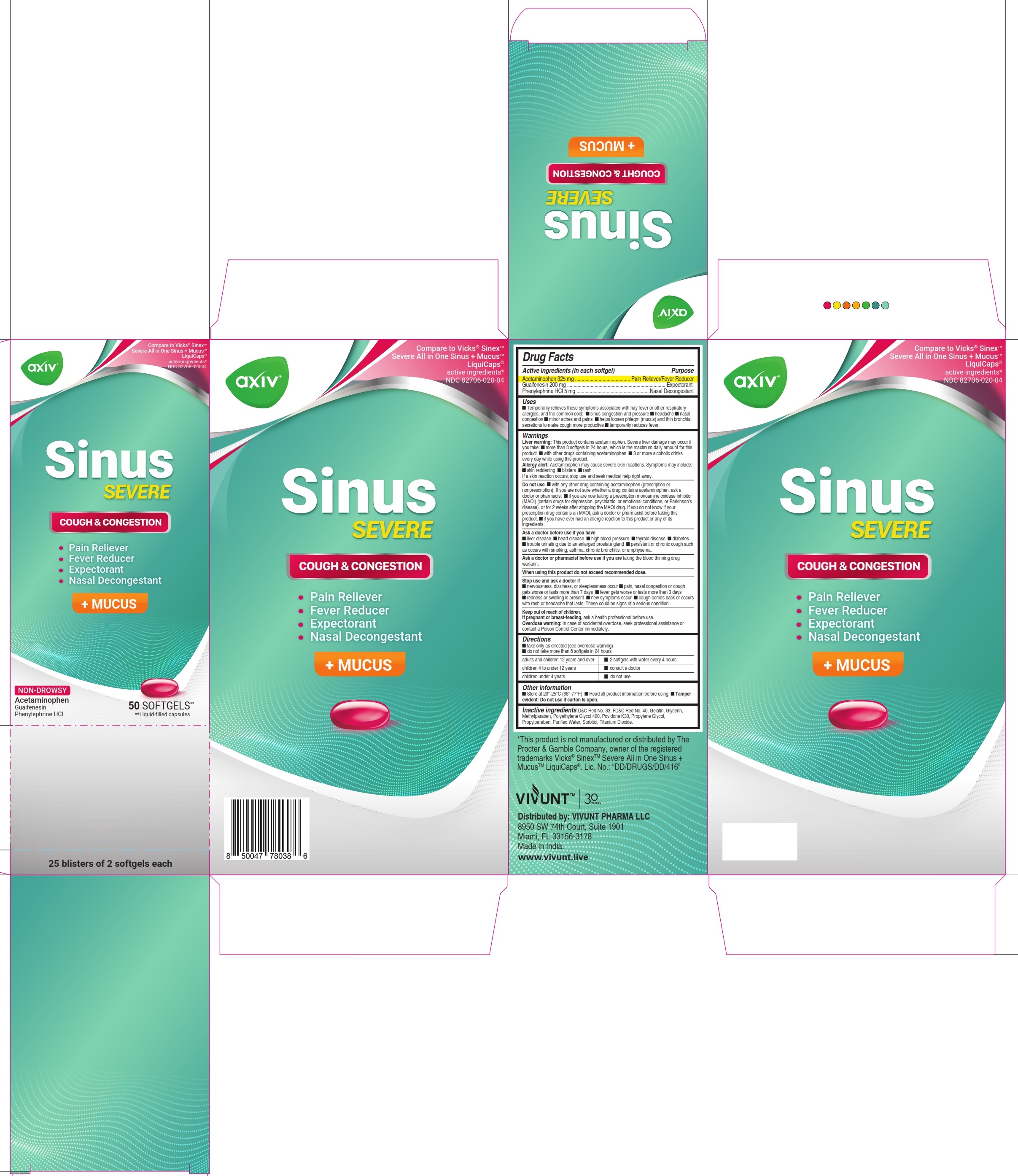 DRUG LABEL: AXIV Sinus Severe Mucus
NDC: 82706-020 | Form: CAPSULE, LIQUID FILLED
Manufacturer: VIVUNT PHARMA LLC
Category: otc | Type: HUMAN OTC DRUG LABEL
Date: 20250917

ACTIVE INGREDIENTS: PHENYLEPHRINE HYDROCHLORIDE 5 mg/1 1; GUAIFENESIN 200 mg/1 1; ACETAMINOPHEN 325 mg/1 1
INACTIVE INGREDIENTS: PROPYLPARABEN; GLYCERIN; FD&C RED NO. 40; D&C RED NO. 33; GELATIN; POLYETHYLENE GLYCOL 400; PROPYLENE GLYCOL; WATER; TITANIUM DIOXIDE; SORBITOL; METHYLPARABEN; POVIDONE K30

AXIV - Sinus Severe + Mucus

Drug Facts

ACTIVE INGREDIENT

Active Ingredients (in each softgel) | Purpose
Acetaminophen 325 mg | Pain reliever-Fever reducer
Guaifenesin 200 mg | Expectorant
Phenylephrine HCl 5 mg | Nasal decongestant

Uses

Temporarily relieves these symptoms associated with hay fever or other respiratory allergies, and the common cold:

- sinus congestion and pressure
- headache
- nasal congestion
- minor aches and pains
- helps loosen phlegm (mucus) and thin bronchial secretions to make coughs more productive
- temporarily reduces fever

Warnings

Liver warning

This product contains acetaminophen. Severe liver damage may occur if you take

- more than 4000 mg of acetaminophen in 24 hours
- with other drugs containing acetaminophen
- 3 or more alcoholic drinks every day while using this product

Allergy Alert:

Allergy alert: Acetaminophen may cause severe skin reactions. Symptoms may include:

- skin reddening
- blisters
- rash

If a skin reaction occurs, stop use and seek medical help right away.

Do not use

- with any other drug containing acetaminophen (prescription or nonprescription). If you are not sure whether a drug contains acetaminophen, ask a doctor or pharmacist.
- if you are now taking a prescription monoamine oxidase inhibitor (MAOI) (certain drugs for depression, psychiatric, or emotional conditions, or Parkinson's disease), or for 2 weeks after stopping the MAOI drug. If you do not know if your prescription drug contains an MAOI, ask a doctor or pharmacist before taking this product.
- if you have ever had an allergic reaction to this product or any of its ingredients

Ask a doctor before use if you have

- liver disease
- heart disease
- high blood pressure
- thyroid disease
- diabetes
- trouble urinating due to an enlarged prostate gland
- persistent or chronic cough such as occurs with smoking, asthma, chronic bronchitis, or emphysema
- cough that occurs with too much phlegm (mucus)

Ask a doctor or pharmacist before use if you are

taking the blood thinning drug warfarin

When using this product

do not exceed recommended dose

Stop use and ask a doctor if

- nervousness, dizziness, or sleeplessness occur
- pain, nasal congestion or cough gets worse or lasts more than 7 days
- fever gets worse or lasts more than 3 days
- redness or swelling is present
- new symptoms occur
- cough comes back or occurs with rash or headache that lasts

These could be signs of a serious condition

Keep out of reach of children

If pregnant or breast-feeding

ask a health professional before use.

Overdose warning

In case of accidental overdose, seek professional assistance or contact a Poison Control Center immediately.

Directions

- Take only as directed (see overdose warning)
- Do not take more than 8 softgels in 24 hours

adults and children 12 years and over | 2 softgels with water every 4 hours
children 4 to under 12 years | consult a doctor
children under 4 years | do not use

Other information

- Store at 20° - 25 °C (68 °- 77 °F)
- Read all product information before using
- Tamper Evident: Do not use if carton is open or blister unit is broken.
- Tamper Evident: Do not use if carton or pouch is open

Inactive ingredients

D&C Red No. 33, FD&C Red No. 40, Gelatin, Glycerin, Methylparaben, Polyethylene Glycol 400, Povidone K30, Propylene Glycol, Propylparaben, Purified Water, Sorbitol, Titanium Dioxide

Distributed by:

VIVUNT PHARMA LLC
8950 SW 74th. Court. Suite 1901

Miami, Florida, 33156-3178

Made in India

www.vivunt.live

PRINCIPAL DISPLAY PANEL-AXIV Sinus Severe + Mucus 100

Compare Vicks® Sinex ™

Severe All In One Sinus + Mucus™ LiquiCaps®

active ingredients*

NDC 82706-020-03

AXIV Sinus Severe + Mucus

Cough & Congestion

Pain Reliever
Fever Reducer
Expectorant
Nassal Decongestant

NON-DROWSY

Acetaminophen, Guaifenesin, Phenylephrine HCl

100 SOFTGELS** **Liquid-filled Capsules

*This product is not manufactured or distributed by

The Procter &Gamble Company, owner of the registered

trademarks Vicks® Sinex ™ Severe All In One Sinus + Mucus™ LiquiCaps®

PRINCIPAL DISPLAY PANEL - AXIV Sinus Severe + Mucus 24

Compare Vicks® Sinex ™

Severe All In One Sinus + Mucus™ LiquiCaps®

active ingredients*

NDC 82706-020-01

AXIV Sinus Severe + Mucus

Cough & Congestion

Pain Reliever
Fever Reducer
Expectorant
Nassal Decongestant

NON-DROWSY

Acetaminophen, Guaifenesin, Phenylephrine HCl

24 SOFTGELS** **Liquid-filled Capsules

*This product is not manufactured or distributed by

The Procter &Gamble Company, owner of the registered

trademarks Vicks® Sinex ™ Severe All In One Sinus + Mucus™ LiquiCaps®

PRINCIPAL DISPLAY PANEL - AXIV Sinus Severe + Mucus 50

Compare Vicks® Sinex ™

Severe All In One Sinus + Mucus™ LiquiCaps®

active ingredients*

NDC 82706-020-04

AXIV Sinus Severe + Mucus

Cough & Congestion

Pain Reliever
Fever Reducer
Expectorant
Nassal Decongestant

NON-DROWSY

Acetaminophen, Guaifenesin, Phenylephrine HCl

50 SOFTGELS** **Liquid-filled Capsules

*This product is not manufactured or distributed by

The Procter &Gamble Company, owner of the registered

trademarks Vicks® Sinex ™ Severe All In One Sinus + Mucus™ LiquiCaps®